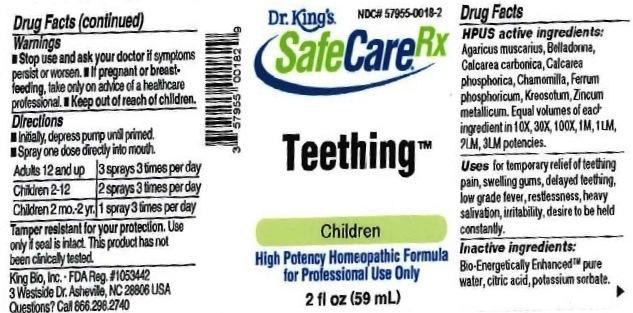 DRUG LABEL: Teething
NDC: 57955-0018 | Form: LIQUID
Manufacturer: King Bio Inc.
Category: homeopathic | Type: HUMAN OTC DRUG LABEL
Date: 20161213

ACTIVE INGREDIENTS: AMANITA MUSCARIA FRUITING BODY 10 [hp_X]/59 mL; ATROPA BELLADONNA 10 [hp_X]/59 mL; OYSTER SHELL CALCIUM CARBONATE, CRUDE 10 [hp_X]/59 mL; TRIBASIC CALCIUM PHOSPHATE 10 [hp_X]/59 mL; MATRICARIA RECUTITA 10 [hp_X]/59 mL; FERROSOFERRIC PHOSPHATE 10 [hp_X]/59 mL; WOOD CREOSOTE 10 [hp_X]/59 mL; ZINC 10 [hp_X]/59 mL
INACTIVE INGREDIENTS: WATER; ANHYDROUS CITRIC ACID; POTASSIUM SORBATE

Teething™

ACTIVE INGREDIENT

Drug Facts__________________________________________________________________________________________________________

HPUS active ingredients: Agaricus muscarius, Belladonna, Calcarea carbonica, Calcarea phosphorica, Chamomilla, Ferrum phosphoricum, Kreosotum, Zincum metallicum. Equal volumes of each ingredient in 10X, 30X, 100X, 1M, 1LM, 2LM, 3LM potencies.

INDICATIONS AND USAGE

Uses for temporary relief of: teething pain, swelling gums, delayed teething, low grade fever, restlessness, heavy salivation, irritability, desire to be held constantly.

Inactive Ingredients:

Bio-Energetically Enhanced™ pure water, citric acid and potassium sorbate.

Warnings

- Stop use and ask your doctor if symptoms persist or worsen.
- If pregnant or breast-feeding, take only on advice of a healthcare professional.

- Keep out of reach of children.

Directions

- Initially, depress pump until primed.
- Spray one dose directly into mouth.
- Adults 12 and up: 3 sprays 3 times per day
- Children 2-12: 2 sprays 3 times per day
- Children 2 mo-2yr: 1 spray 3 times per day

OTHER SAFETY INFORMATION

Tamper resistant for your protection. Use only if safety seal is intact. This product has not been clinically tested.

PURPOSE

Uses for temporary relief of:

- teething pain
- swelling gums
- delayed teething
- low grade fever
- restlessness
- heavy salivation
- irritability
- desire to be held constantly